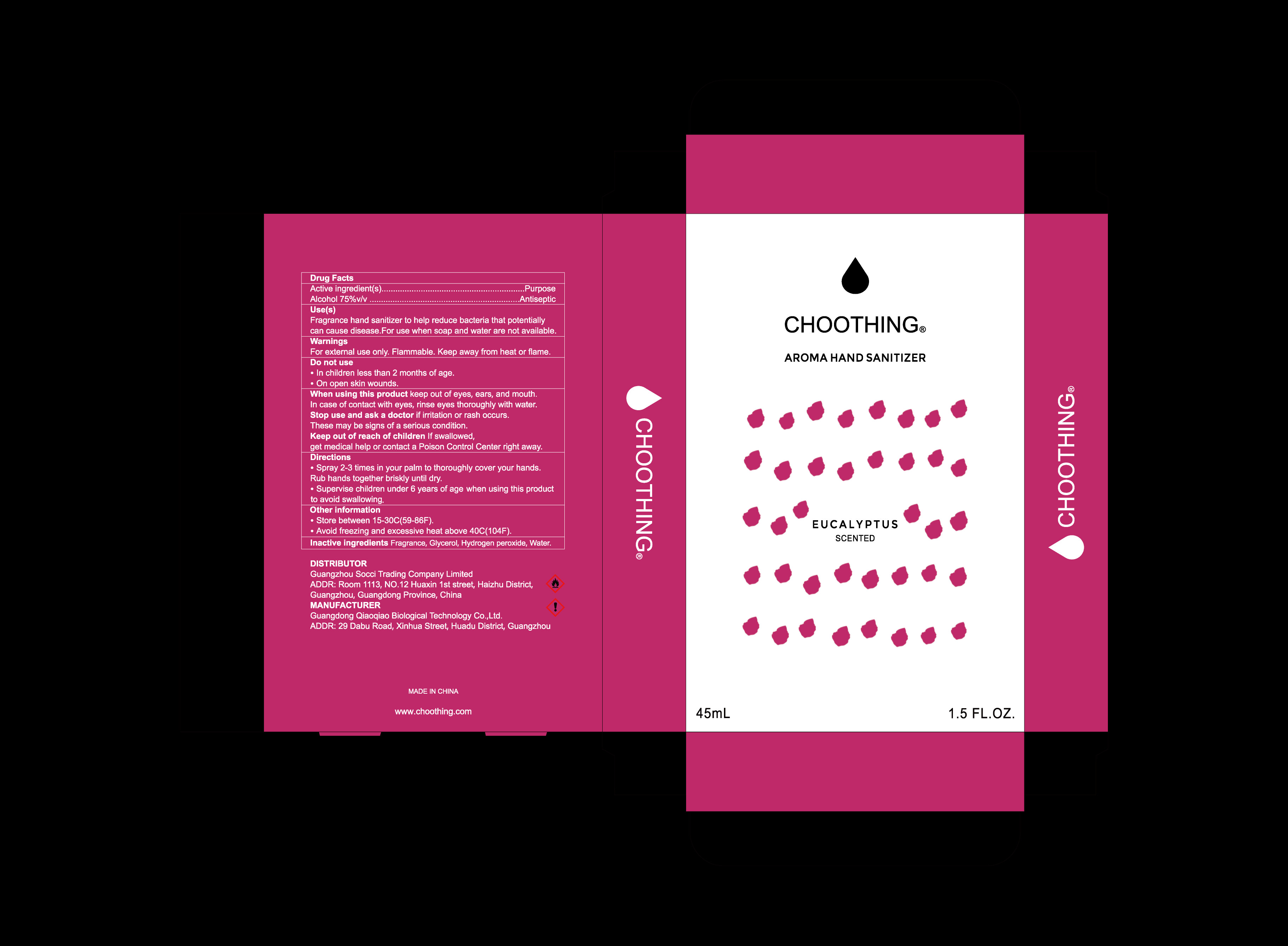 DRUG LABEL: AROMA HAND SANITIZER
NDC: 55036-001 | Form: LIQUID
Manufacturer: Guangzhou Socci Trading Company Limited
Category: otc | Type: HUMAN OTC DRUG LABEL
Date: 20210114

ACTIVE INGREDIENTS: ALCOHOL 75 mL/100 mL
INACTIVE INGREDIENTS: WATER; P-ANISALDEHYDE; GLYCERIN; HYDROGEN PEROXIDE

ACTIVE INGREDIENT

Alcohol 75%

PURPOSE

Antiseptic

Use(s)

Fragrance hand sanitizer to help reduce bacteria that potentially can cause disease.For use when soap and water are not available.

WARNINGS

For external use only. Flammable. Keep away from heat or flame.

DO NOT USE

ln children less than 2 months of age.

On open skin wounds.

When using this product keep out of eyes, ears, and mouth.ln case of contact with eyes,rinse eyes thoroughly with water.

Stop use and ask a doctor if irritation or rash occurs.These may be signs of a serious condition.

Keep out of reach of children.If swallowed,get medical help or contact a Poison Control Center right away.

Directions

- Spray 2-3 times in your palm to thoroughly cover your hands.Rub hands together briskly until dry.
- Supervise children under 6 years of age when using this product to avoid swallowing.

Other information

- Store between 15-30°C(59-86°F).
- Avoid freezing and excessive heat above 40°C(104°F).

INACTIVE INGREDIENT

Fragrance, Glycerol, Hydrogen peroxide, Water.